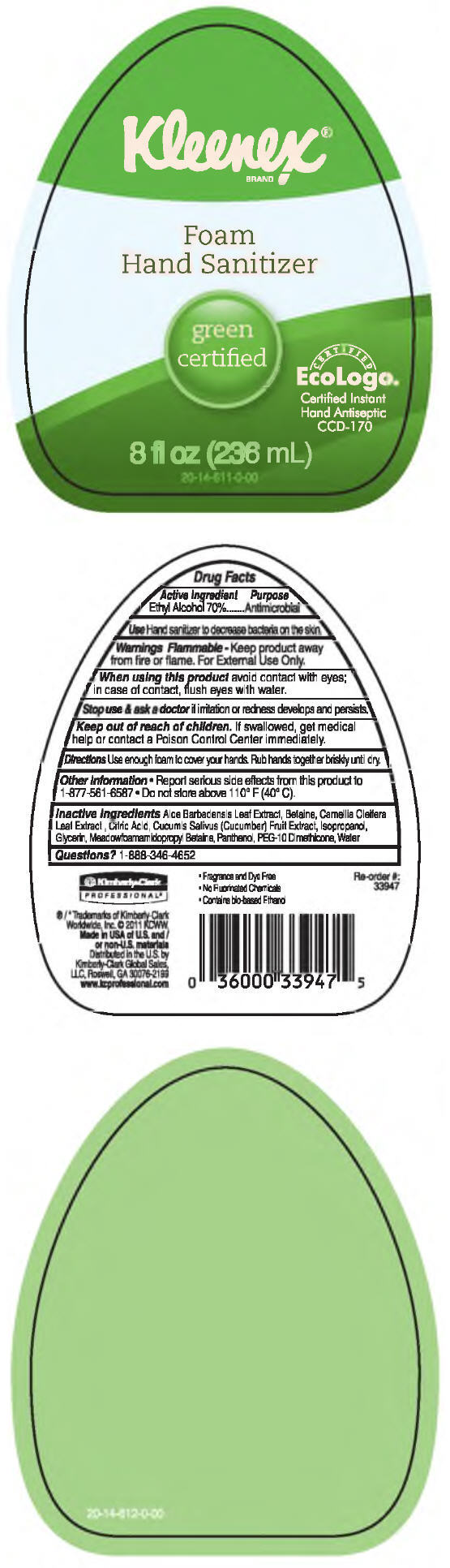 DRUG LABEL: Kleenex Hand Sanitizer, Green Certified
NDC: 55118-535 | Form: SOLUTION
Manufacturer: Kimberly-Clark Corporation
Category: otc | Type: HUMAN OTC DRUG LABEL
Date: 20141104

ACTIVE INGREDIENTS: Alcohol 70 mL/100 mL
INACTIVE INGREDIENTS: Water; Isopropyl Alcohol; Betaine; Citric Acid Monohydrate; Panthenol; Glycerin; Aloe Vera Leaf; Camellia Oleifera Leaf; Cucumber

Kleenex Foam Hand Sanitizer, Green Certified

Drug Facts

Active Ingredient

Ethyl Alcohol 70%

Purpose

Antimicrobial

Use

Hand sanitizer to decrease bacteria on the skin.

Warnings

Flammable - Keep product away from fire or flame. For External Use Only.

When using this product avoid contact with eyes; in case of contact, flush eyes with water.

Stop use & ask a doctor if irritation or redness develops and persists.

Keep out of reach of children. If swallowed, get medical help or contact a Poison Control Center immediately.

Directions

Use enough foam to cover your hands. Rub hands together briskly until dry.

Other Information

- Report serious side effects from this product to 1-877-561-6587
- Do not store above 110° F (40° C).

Inactive Ingredients

Aloe Barbadensis Leaf Extract, Betaine, Camellia Oleifera Leaf Extract, Citric Acid, Cucumis Sativus (Cucumber) Fruit Extract, Isopropanol, Glycerin, Meadowfoamamidopropyl Betaine, Panthenol, PEG-10 Dimethicone, Water

Questions?

1-888-346-4652

Distributed in the U.S. by
Kimberly-Clark Global Sales,
LLC, Roswell, GA 30076-2199

PRINCIPAL DISPLAY PANEL - 236 mL Bottle Label

Kleenex®
BRAND

Foam
Hand Sanitizer

green
certified

CERTIFIED
EcoLogo®
Certified Instant
Hand Antiseptic
CCD-170

8 fl oz (236 mL)

20-14-611-0-00